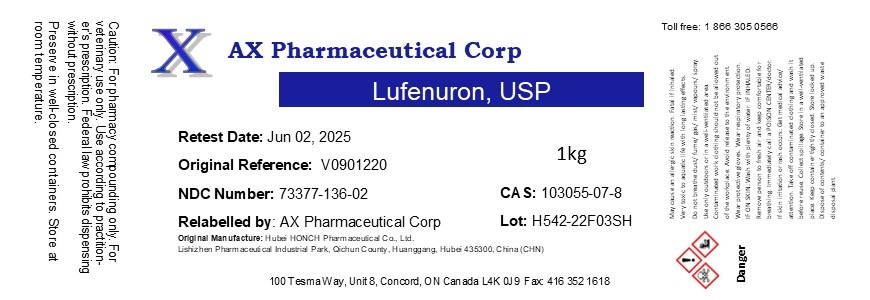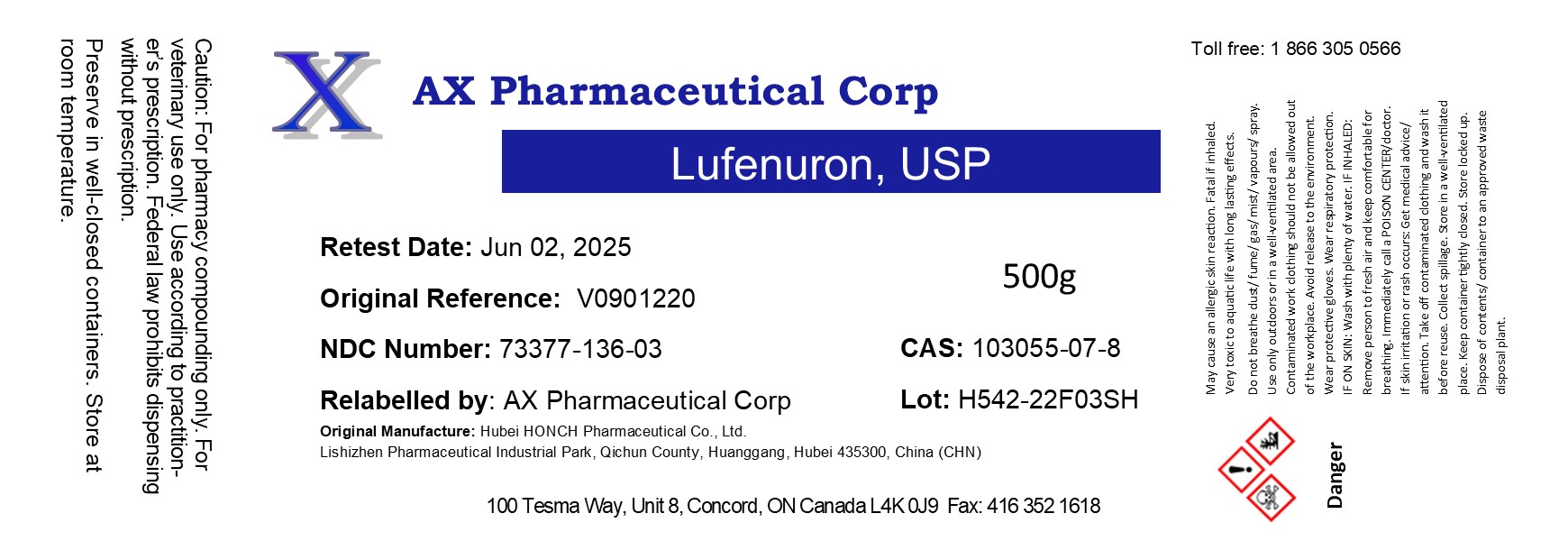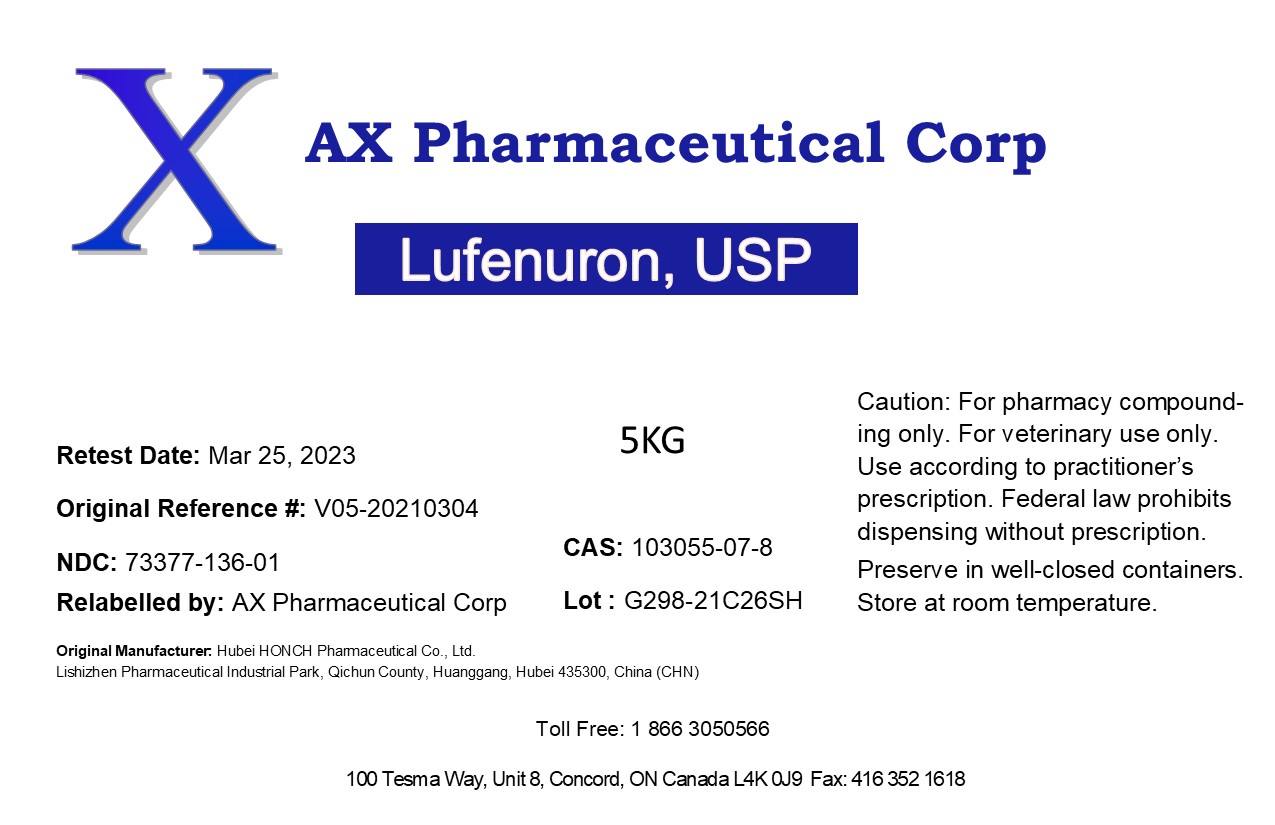 DRUG LABEL: Lufenuron
NDC: 73377-136 | Form: POWDER
Manufacturer: AX Pharmaceutical Corp
Category: other | Type: BULK INGREDIENT - ANIMAL DRUG
Date: 20241128

ACTIVE INGREDIENTS: LUFENURON 1 kg/1 kg

Lufenuron